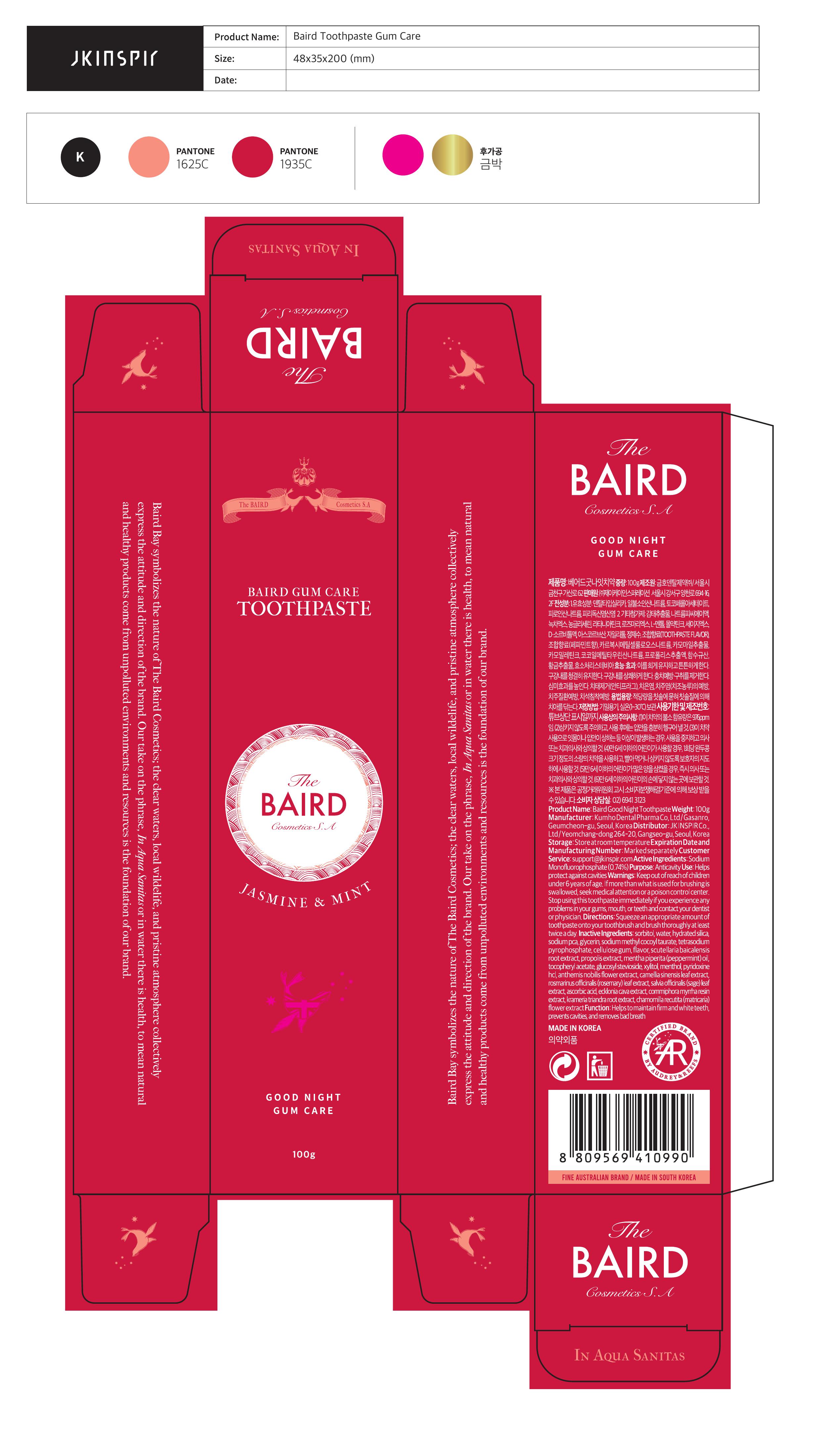 DRUG LABEL: Baird Good Night
NDC: 81239-100 | Form: PASTE, DENTIFRICE
Manufacturer: JK INSPIR Co., Ltd
Category: otc | Type: HUMAN OTC DRUG LABEL
Date: 20210317

ACTIVE INGREDIENTS: SODIUM FLUORIDE 0.74 g/100 g; SODIUM MONOFLUOROPHOSPHATE 0.0976 g/100 g
INACTIVE INGREDIENTS: WATER

Baird Good Night Toothpaste

active ingredient

Sodium Monofluorophosphate (0.74%)

Keep out of reach of children under 6 years of age.

If more than what is used for brushing is swallowed, get medical help or contact a Poison Control Center (1-800-222-1222) right

away.

Purpose

Helps protect against cavities

Uses

Helps protect against cavities

Warnings

Stop use and ask a doctor if you experience any problems in your gums, mouth, or teeth.

Directions

Adults and children 2 years of age and older

Brush tooth thoroughly, preferably after each meal, or at least

twice a day, or as directed by your dentist. Do not swallow.

Children 2 to 6 years

To minimize swallowing, use a pea-sized amount and

supervising brushing until good habits are established.

Children under 2 years

Ask a dentist or physician

Inactive Ingredients

Sorbitol, water, hydrated silica, sodium pca, glycerin, sodium methylcocoytaurate,

tetrasodium pyrophosphate, cellulose gum, flavor, scutellaria baicalensis root extract,

propolis extract, mentha piperita (peppermint) oil, tocopherylacetate, glucosylstevioside,

xylitol, menthol, pyridoxine hcl, anthemis nobilis flower extract, camellia sinensis leaf extract,

Rosmarinus officinalis (rosemary) leaf extract, salvia officinalis (sage) leaf extract, ascorbic

acid, ecklonia cava extract, commiphora myrrha resin extract, krameria triandra root extract,

chamomilla recutita (matricaria) flower extract

Other Information

Store at room temperature